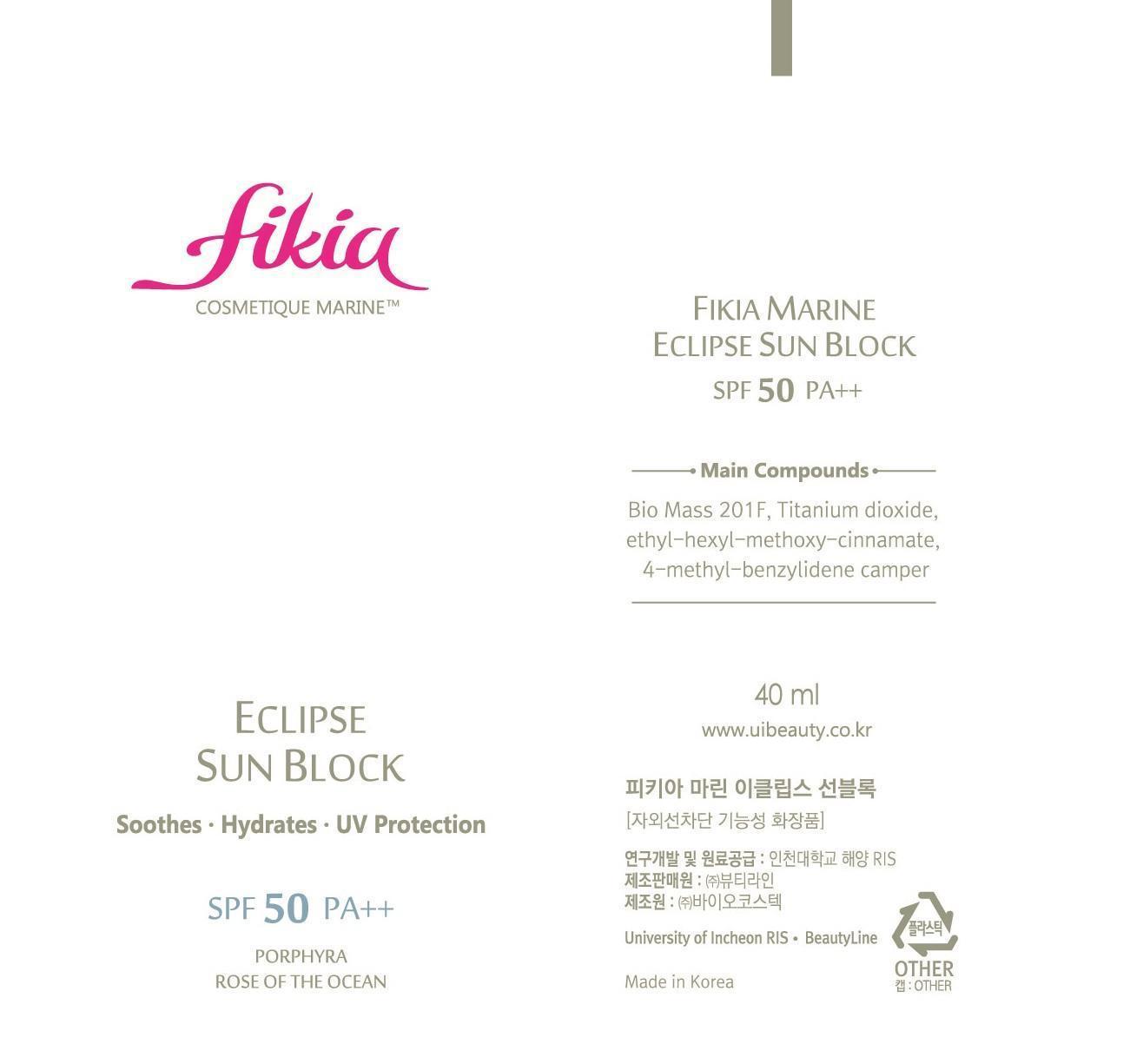 DRUG LABEL: Fikia Marine Eclipse Sun Block SPF 50 PA
NDC: 69327-3001 | Form: CREAM
Manufacturer: Beauty Line Co., Ltd.
Category: otc | Type: HUMAN OTC DRUG LABEL
Date: 20141025

ACTIVE INGREDIENTS: TITANIUM DIOXIDE 5 g/100 mL
INACTIVE INGREDIENTS: WATER; BUTYLENE GLYCOL; HYALURONATE SODIUM

Drug Facts

ACTIVE INGREDIENT

titanium dioxide

INACTIVE INGREDIENT

water, glycerin, zinc oxide, bentonite, sodium chloride, butylene glycol, disodium edta, fragrance, etc

PURPOSE

protect the skin againse the harmful UV rays

keep out or reach of the children

INDICATIONS AND USAGE

apply evenly on exposed areas after daily skin-care routine

WARNINGS

-If in contact with the eyes, wash out thoroughty with water If the symptoms are servere, seek medical advice immediately
-This product is for exeternal use only. Do not use for internal use
-If possible, avoid direct sunlight and store in cool and area of low humidity
-In order to maintain the quality of the product and avoid misuse
-Avoid placing the product near fire and store out in reach of children

DOSAGE AND ADMINISTRATION

for external use only